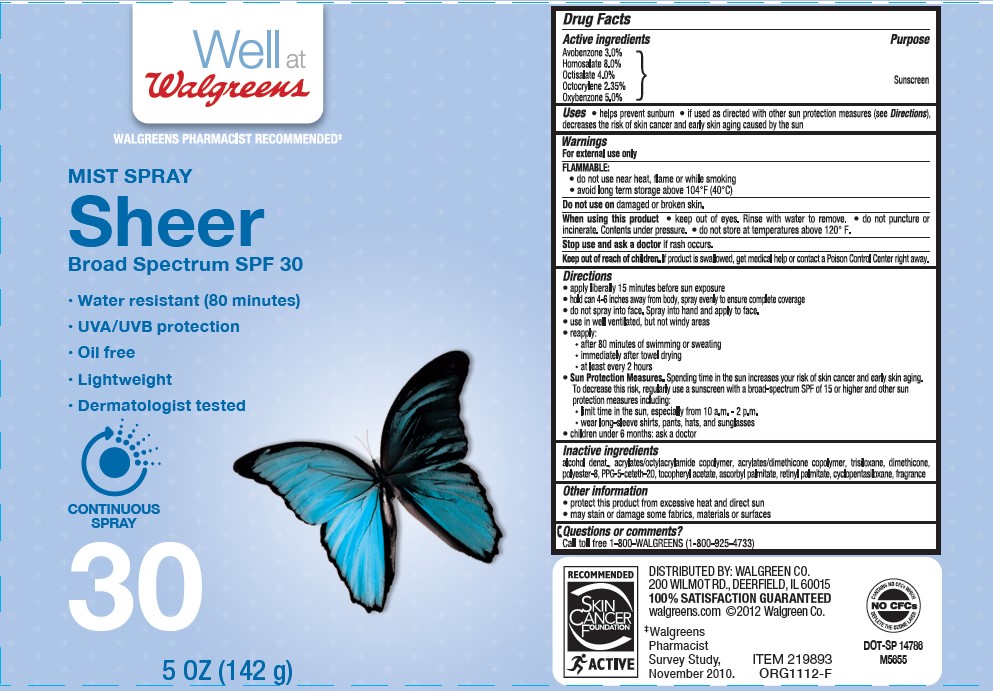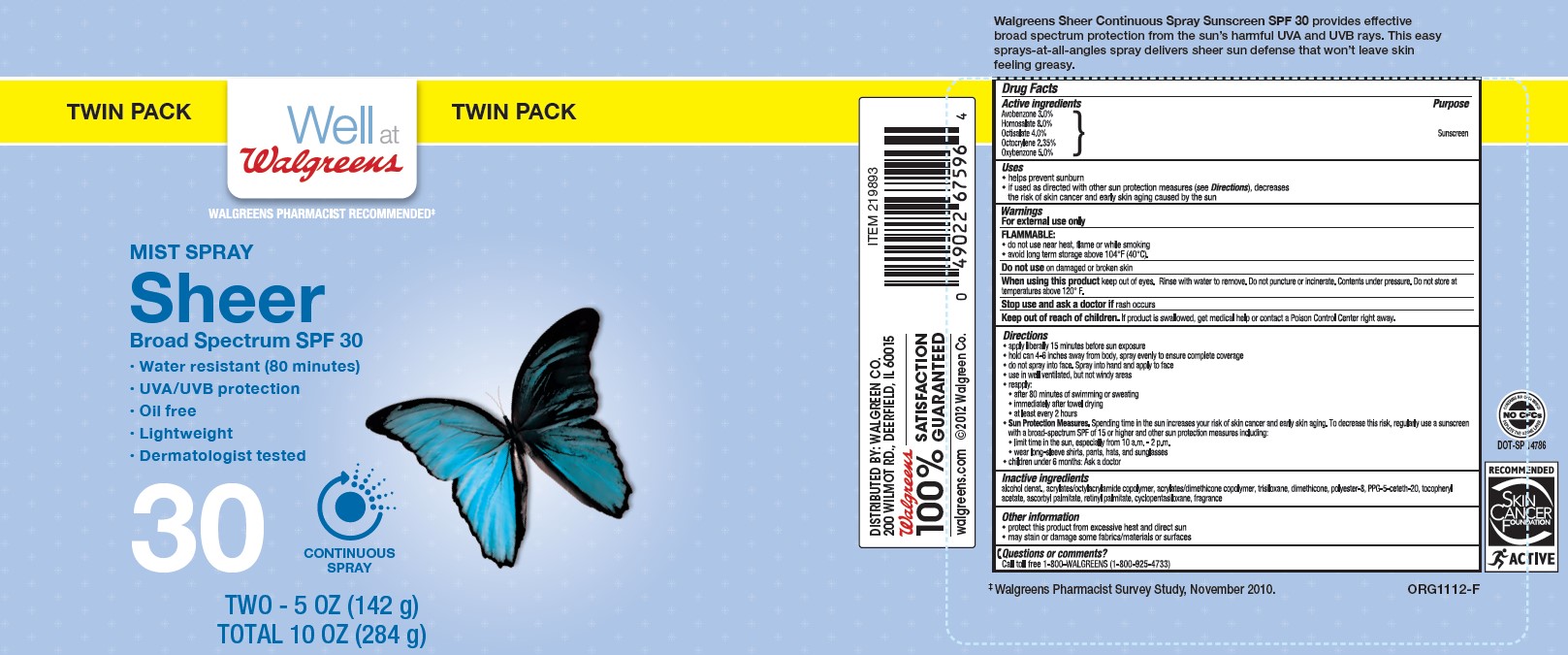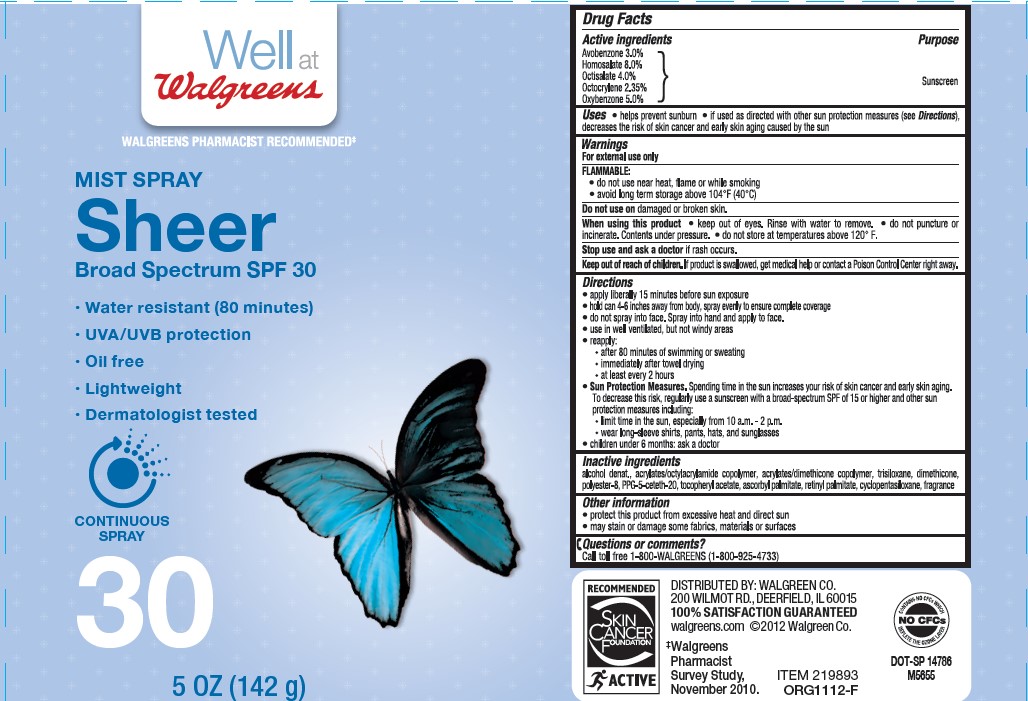 DRUG LABEL: Well at Walgreens Mist Sheer Broad Spectrum Broad Spectrum SPF 30
NDC: 0363-0996 | Form: SPRAY
Manufacturer: WALGREEN COMPANY
Category: otc | Type: HUMAN OTC DRUG LABEL
Date: 20241014

ACTIVE INGREDIENTS: AVOBENZONE 300 mg/10 g; HOMOSALATE 800 mg/10 g; OCTISALATE 400 mg/10 g; OCTOCRYLENE 235 mg/10 g; OXYBENZONE 500 mg/10 g
INACTIVE INGREDIENTS: DIMETHICONE; PPG-5-CETETH-20; VITAMIN A PALMITATE; ALCOHOL; ACRYLATE/ISOBUTYL METHACRYLATE/N-TERT-OCTYLACRYLAMIDE COPOLYMER (75000 MW); CYCLOMETHICONE 5; TRISILOXANE; POLYESTER-8 (1400 MW, CYANODIPHENYLPROPENOYL CAPPED); .ALPHA.-TOCOPHEROL ACETATE; ASCORBYL PALMITATE

Well at Walgreens Mist Spray Sheer Broad Spectrum Broad Spectrum SPF 30

Active ingredients

Avobenzone 3.0%, Homosalate 8.0%, Octisalate 4.0%, Octocrylene 2.35%, Oxybenzone 5.0%

Purpose

Sunscreen

Uses

- helps prevent sunburn
- if used as directed with other sun protection measures (see Directions), decreases the risk of skin cancer and early skin aging caused by the sun

Warnings

For external use only

FLAMMABLE:

• do not use near heat, flame or while smoking
• avoid long term storage above 104°F (40°C)

Do not use

- on damaged or broken skin

When using this product

• keep out of eyes. Rinse with water to remove. • do not puncture or incinerate. Contents under pressure. • do not store at temperatures above 120° F.

Stop use and ask doctor

if rash occurs.

Keep out of reach of children.

If product is swallowed, get medical help or contact a Poison Control Center right away.

Directions

• apply liberally 15 minutes before sun exposure
• hold can 4-6 inches away from body, spray evenly to ensure complete coverage
• do not spray into face. Spray into hand and apply to face.
• use in well ventilated, but not windy areas
• reapply:
• after 80 minutes of swimming or sweating
• immediately after towel drying
• at least every 2 hours

- children under 6 months: Ask a doctor

- Sun Protection Measures. Spending time in the sun increases your risk of skin cancer and early skin aging. To decrease this risk, regularly use a sunscreen with a Broad Spectrum SPF value of 15 or higher and other sun protection measures including:

• limit time in the sun, especially from 10 a.m. - 2 p.m.
• wear long-sleeved shirts, pants, hats, and sunglasses

Inactive ingredients

alcohol denat.,acrylates/octylacrylamide copolymer, acrylates/dimethicone copolymer, trisiloxane, dimethicone, polyester-8, PPG-5-ceteth-20, tocopherol acetate, ascorbyl palmitate, retinyl palmitate, cyclopentasiloxane, fragrance

Other Information

• protect the product in this container from excessive heat and direct sun
• may stain or damage some fabrics, materials or surfaces